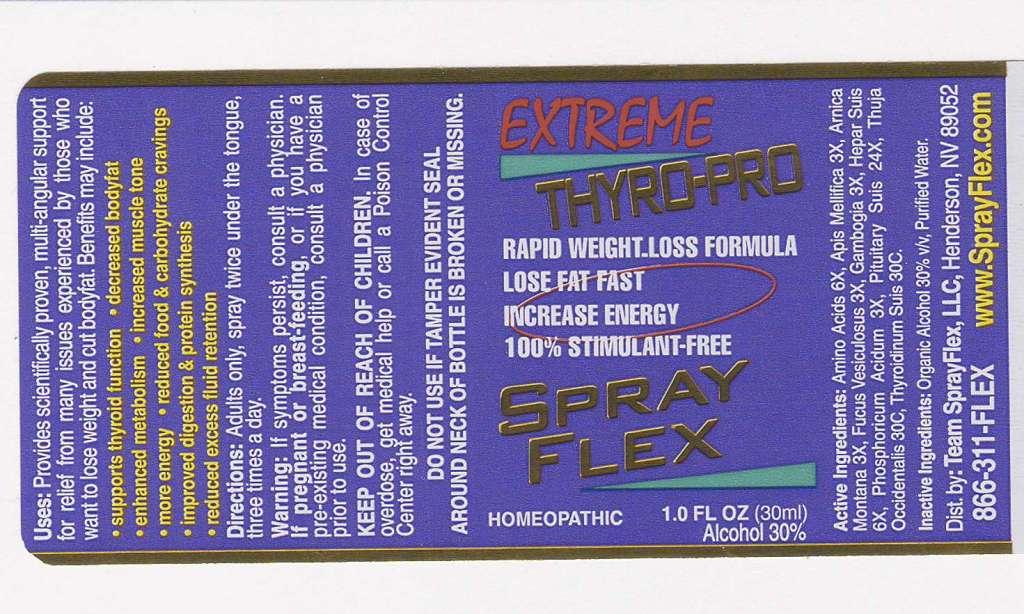 DRUG LABEL: Extreme Thyro pro
NDC: 50845-0039 | Form: SPRAY
Manufacturer: Liddell Laboratories
Category: homeopathic | Type: HUMAN OTC DRUG LABEL
Date: 20100820

ACTIVE INGREDIENTS: AMINO ACIDS 6 [hp_X]/1 mL; APIS MELLIFERA 3 [hp_X]/1 mL; ARNICA MONTANA 3 [hp_X]/1 mL; FUCUS VESICULOSUS 3 [hp_X]/1 mL; GAMBOGE 3 [hp_X]/1 mL; PORK LIVER 6 [hp_X]/1 mL; PHOSPHORIC ACID 3 [hp_X]/1 mL; SUS SCROFA PITUITARY GLAND 24 [hp_X]/1 mL; THUJA OCCIDENTALIS LEAFY TWIG 30 [hp_C]/1 mL; THYROID 30 [hp_C]/1 mL
INACTIVE INGREDIENTS: WATER; ALCOHOL

Extreme Thyro-pro

ACTIVE INGREDIENT

ACTIVE INGREDIENTS: Amino acids 6X, Apis mellifica 3X, Arnica montana 3X, Fucus vesiculosus 3X, Gambogia 3X, Hepar suis 6X, Phosphoricum acidum 3X, Pituitary suis 24X, Thuja occidentalis 30C, Thyroidinum 30C.

PURPOSE

USES: Provides scientifically proven, multi-angular support for relief from many issues experienced by those who want to lose weight and cut bodyfat. Benefits may include: *Supports thyroid function *decreased bodyfat *enhanced metabolism *increased muscle tone *more energy *reduced food and carbohydrate cravings *improved digestion and protein synthesis *reduced excess fluid retention

WARNINGS

WARNINGS: If symptoms persist, consult a physician. If pregnant or breast-feeding, or if you have a pre-existing medical condition, consult a physician prior to use.

DO NOT USE IF TAMPER EVIDENT SEAL AROUND NECK OF BOTTLE IS BROKEN OR MISSING.

DOSAGE AND ADMINISTRATION

DIRECTIONS: Adults only, spray twice under the tongue, three times a day.

INACTIVE INGREDIENT

INACTIVE INGREDIENTS: Organic alcohol 30% v/v, Purified water.

KEEP OUT OF REACH OF CHILDREN: In case of overdose, get medical help or call a Poison Control Center right away.

INDICATIONS AND USAGE

USES: Provides scientifically proven, multi-angular support for relief from many issues experienced by those who want to lose weight and cut bodyfat. Benefits may include: *supports thyroid function *decreased bodyfat *enhanced metabolism *increased muscle tone *more energy *reduced food and carbohydrate cravings *improved digestion and protein synthesis *reduced excess fluid retention

QUESTIONS

Dist. by:

Team SprayFlex, LLC

Henderson, NV 89052

866-311-FLEX

www.SprayFlex.com

PACKAGE LABEL

EXTREME THYRO-PRO

RAPID WEIGHT-LOSS FORMULA

LOSE FAT FAST

INCREASE ENERGY

100% STIMULANT-FREE

SPRAY FLEX

HOMEOPATHIC

1.0 FL OZ (30 ml)